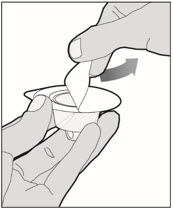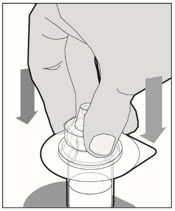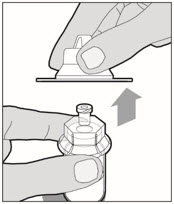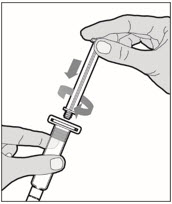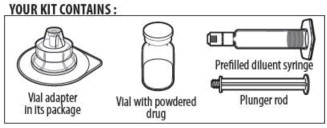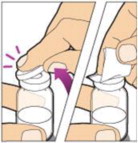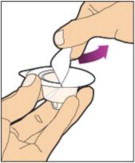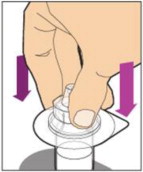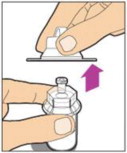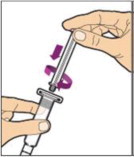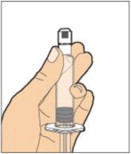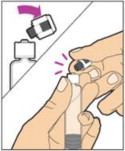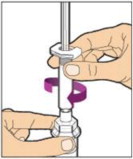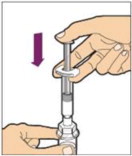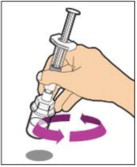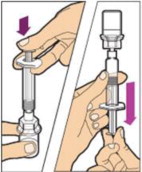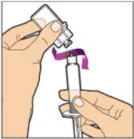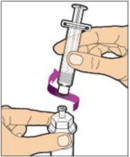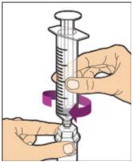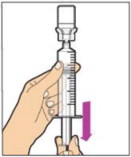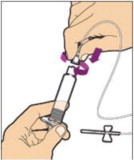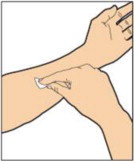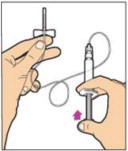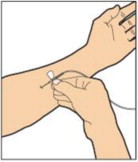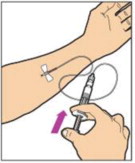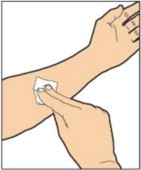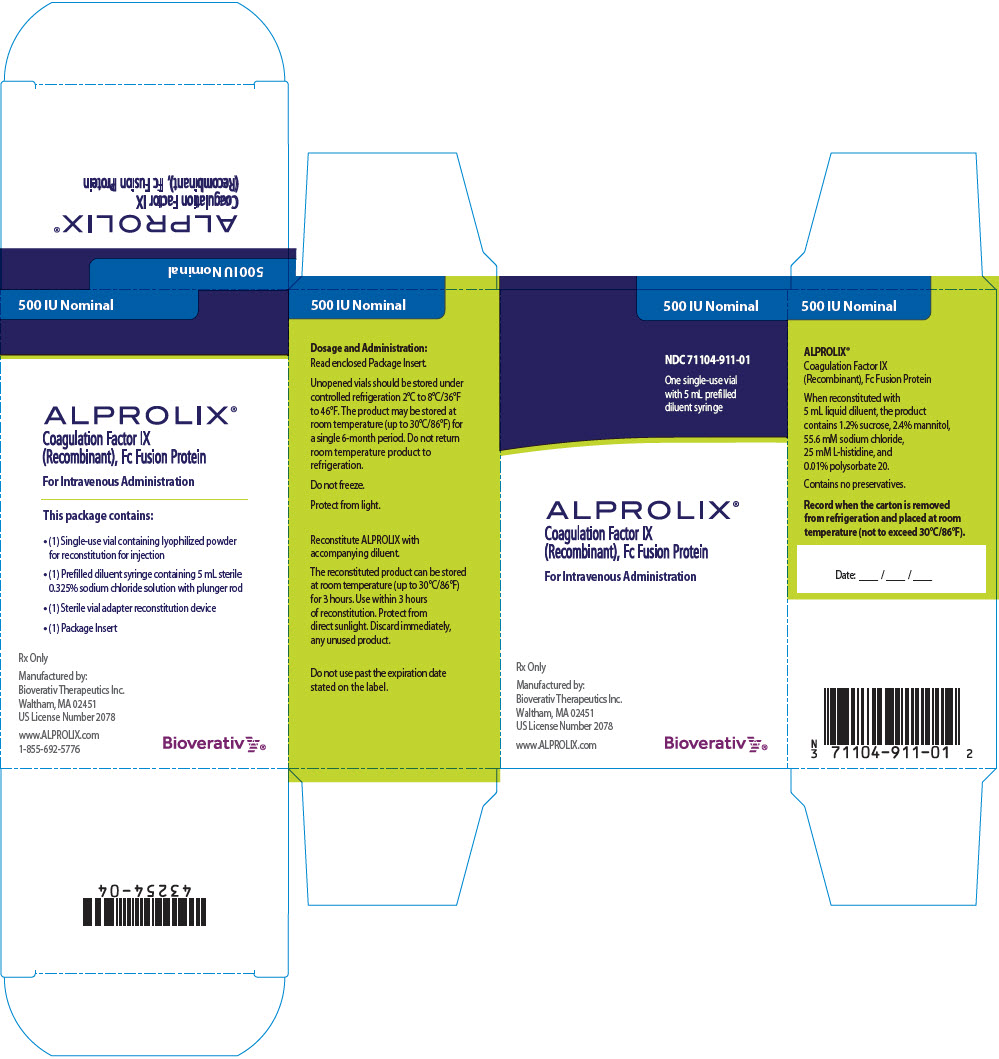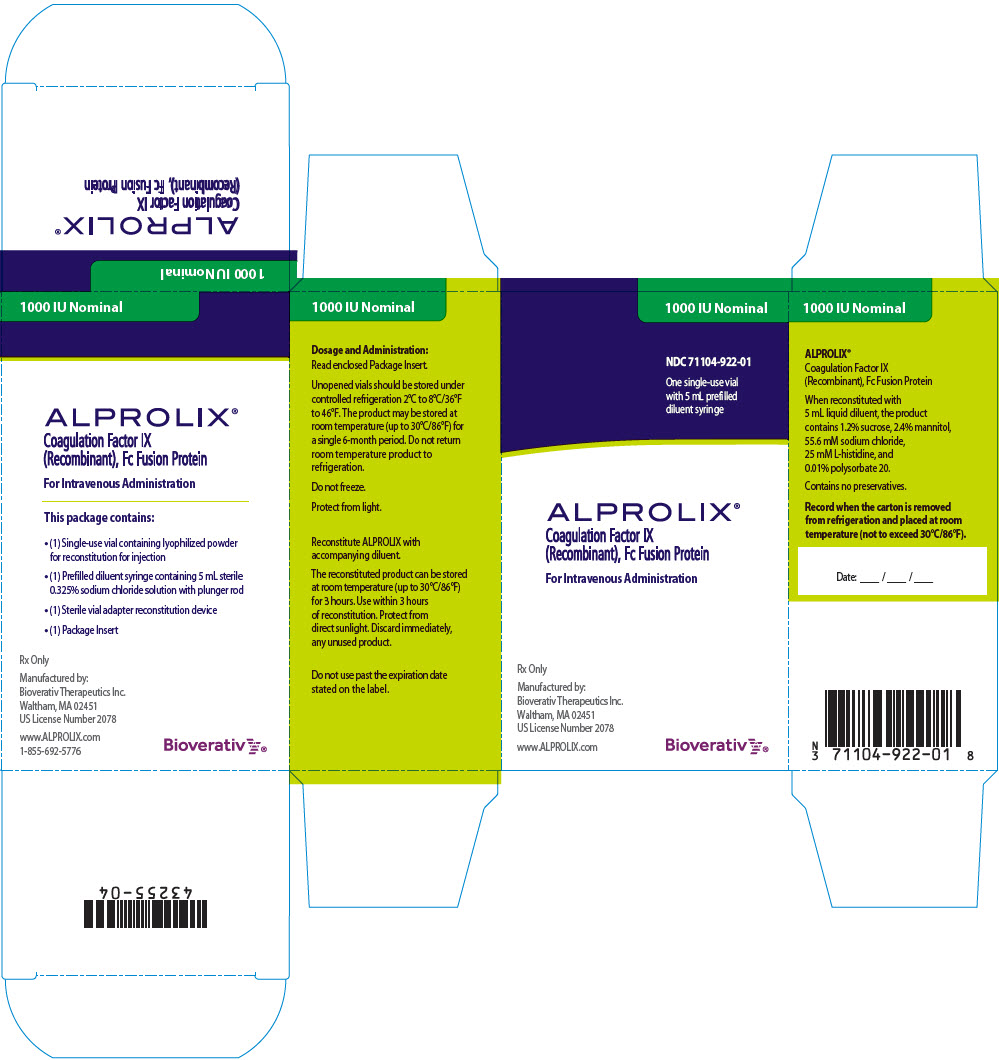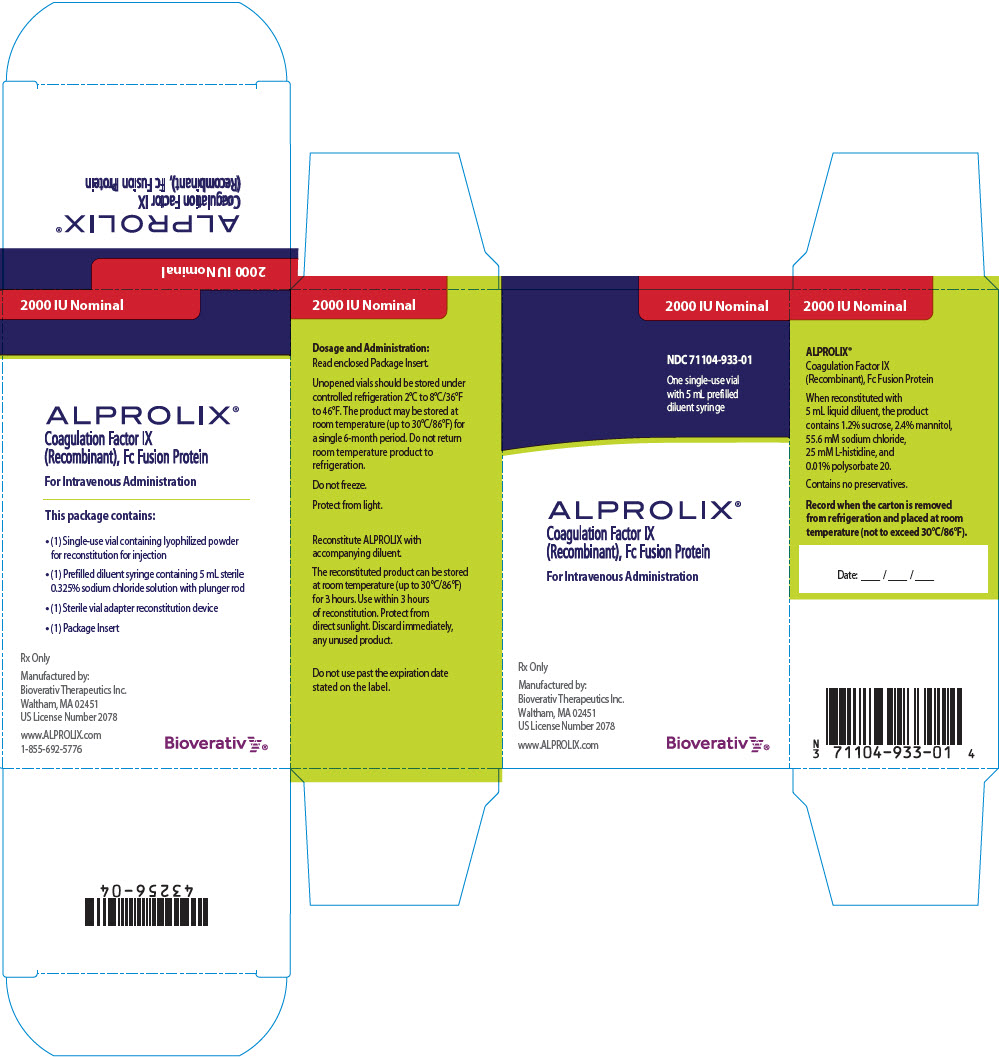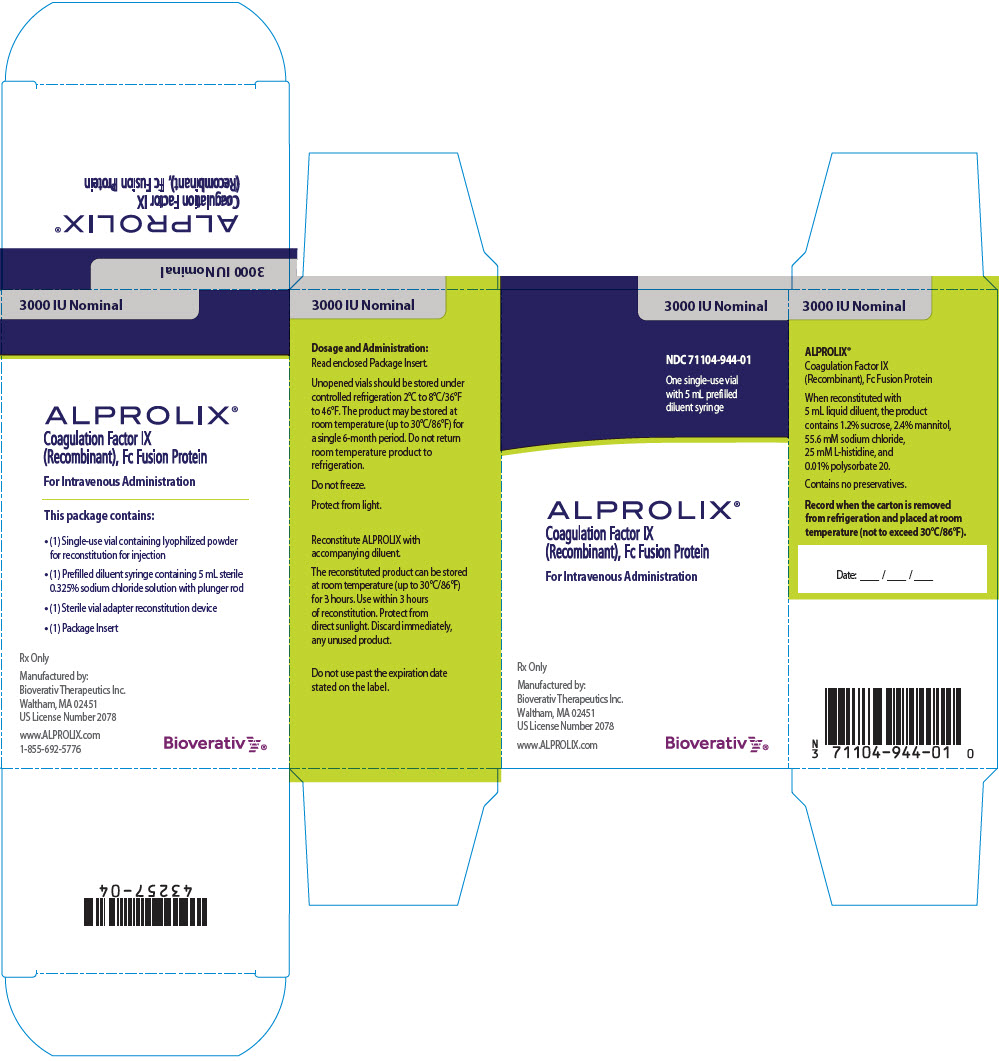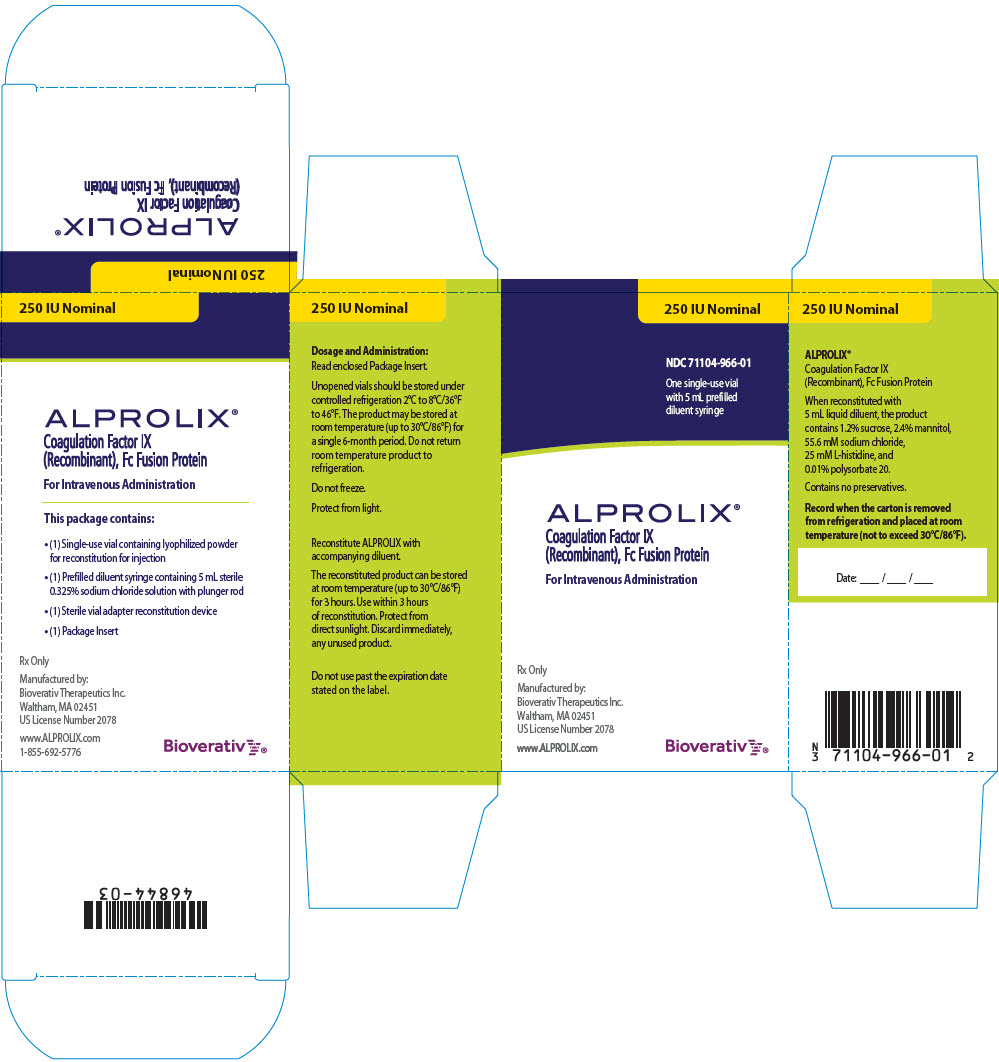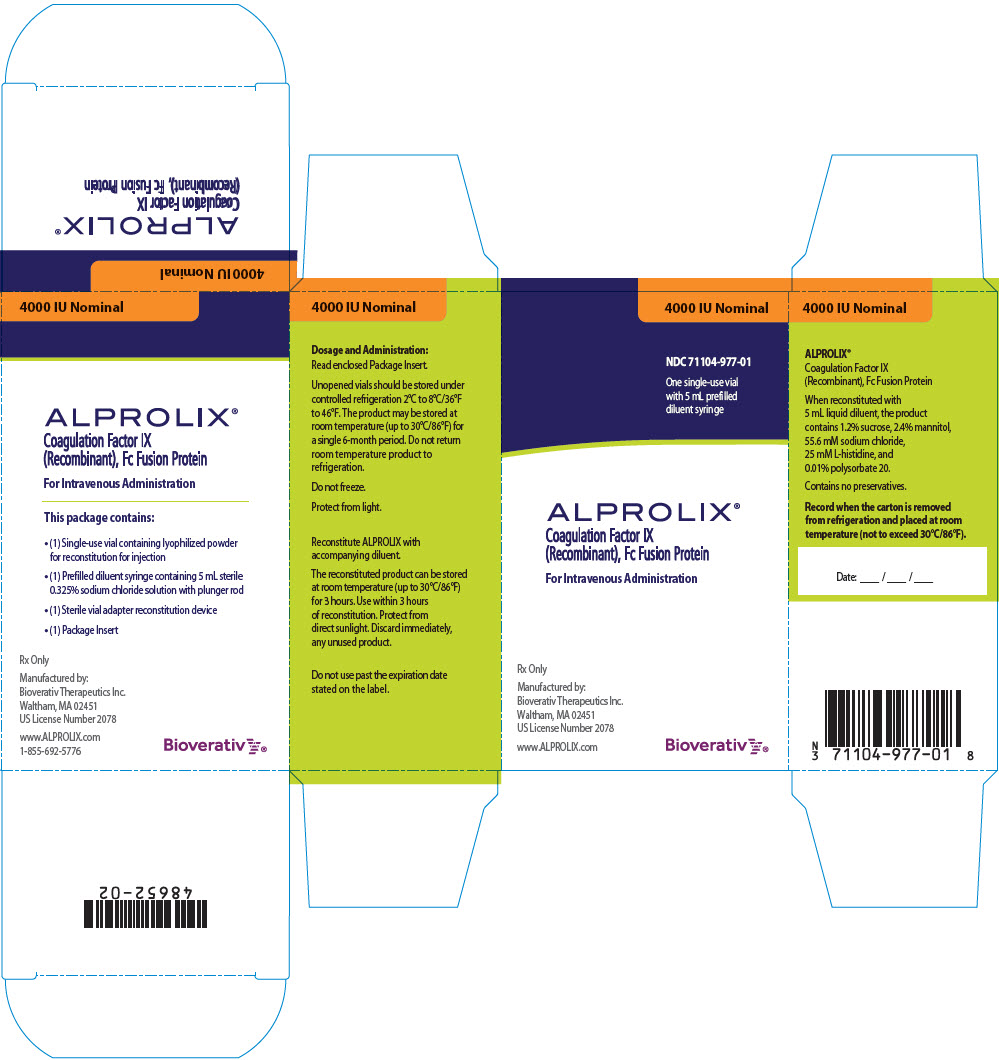 DRUG LABEL: ALPROLIX
NDC: 71104-911 | Form: KIT | Route: INTRAVENOUS
Manufacturer: Bioverativ Therapeutics Inc.
Category: other | Type: PLASMA DERIVATIVE
Date: 20240516

ACTIVE INGREDIENTS: EFTRENONACOG ALFA 500 [iU]/5 mL
INACTIVE INGREDIENTS: HISTIDINE; MANNITOL; SUCROSE; POLYSORBATE 20; SODIUM CHLORIDE

HIGHLIGHTS OF PRESCRIBING INFORMATION

These highlights do not include all the information needed to use ALPROLIX® safely and effectively. See full prescribing information for ALPROLIX.
ALPROLIX® [coagulation factor IX (recombinant), Fc fusion protein], lyophilized powder for solution for intravenous injection.
Initial U.S. Approval: 2014

1 INDICATIONS AND USAGE

ALPROLIX, Coagulation Factor IX (Recombinant), Fc Fusion Protein, is a recombinant DNA derived coagulation Factor IX concentrate indicated in adults and children with hemophilia B for:

- On-demand treatment and control of bleeding episodes,
- Perioperative management of bleeding,
- Routine prophylaxis to reduce the frequency of bleeding episodes.

Limitation of Use:

ALPROLIX is not indicated for induction of immune tolerance in patients with hemophilia B. (1)

2 DOSAGE AND ADMINISTRATION

For intravenous use after reconstitution only.

On-demand treatment and control of bleeding episodes:

- Each vial of ALPROLIX contains the labeled amount of coagulation Factor IX potency in international units (IU). (2.1)
- On average, one unit per kilogram body weight of ALPROLIX increased the circulating Factor IX level by approximately 1% (IU/dL) in adults and children ≥6 years of age and by 0.6% (IU/dL) in children under 6 years of age. (2.1)

Initial Dose: Type of Bleeding | Target Circulating FIX (IU/dL) | Dosing Interval (hours)
Minor and Moderate | 30–60 | Repeat every 48 hours as needed if there is further evidence of bleeding.
Major | 80–100 | Consider repeat dose after 6–10 hours, then every 24 hours for 3 days, then every 48 hours until healing achieved.

Perioperative management:

- Minor surgery: a single infusion to reach FIX level of 50–80 IU/dL may be sufficient. Repeat as needed after 24–48 hours until bleeding stops and healing is achieved. (2.1)
- Major surgery: initial infusion to reach FIX level of 60–100 IU/dL. Consider a repeat dose after 6–10 hours and then every 24 hours for the first 3 days, then every 48 hours until bleeding stops and healing is achieved. (2.1)

Routine prophylaxis:

For adults and adolescents ≥12 years of age, start at 50 IU/kg once weekly or 100 IU/kg once every 10 days. For children <12 years of age, start at 60 IU/kg once weekly. Adjust dosing regimen based on individual response. More frequent or higher doses may be needed in children <12 years of age. (2.1)

3 DOSAGE FORMS AND STRENGTHS

ALPROLIX is available as a lyophilized powder in single-dose vials containing nominally 250, 500, 1000, 2000, 3000, or 4000 international units (IU). (3)

4 CONTRAINDICATIONS

Do not use in individuals who have a known history of hypersensitivity reactions, including anaphylaxis, to the product or its excipients. (4)

5 WARNINGS AND PRECAUTIONS

- Hypersensitivity reactions, including anaphylaxis, have been reported. Should symptoms occur, discontinue ALPROLIX and administer appropriate treatment. (5.1)
- Neutralizing antibodies (inhibitors) to FIX have been reported with ALPROLIX. Perform an assay that measures Factor IX inhibitor concentration if plasma Factor IX level fails to increase as expected or if bleeding is not controlled with an appropriate dose. (5.2, 5.4)
- The use of Factor IX products has been associated with the development of thromboembolic complications. (5.3)
- Nephrotic syndrome has been reported following immune tolerance induction with Factor IX-containing products in hemophilia B patients with Factor IX inhibitors and a history of allergic reactions to Factor IX. (5.5)

6 ADVERSE REACTIONS

Previously Treated Patients (PTPs): Common adverse reactions (incidence ≥1%) from clinical trials were headache, oral paresthesia, and obstructive uropathy. (6)

Previously Untreated Patients (PUPs): Common adverse reactions (incidence ≥1%) from clinical trial were Factor IX inhibition, injection site erythema, and hypersensitivity. (6)

To report SUSPECTED ADVERSE REACTIONS, contact Bioverativ Therapeutics Inc. at 1-855-692-5776 or FDA at 1-800-FDA-1088 or www.fda.gov/medwatch.

8 USE IN SPECIFIC POPULATIONS

Pediatric: Higher dose per kilogram body weight or more frequent dosing may be needed in patients <12 years of age. (8.4)

FULL PRESCRIBING INFORMATION

1 INDICATIONS AND USAGE

ALPROLIX, Coagulation Factor IX (Recombinant), Fc Fusion Protein, is a recombinant DNA derived coagulation Factor IX concentrate indicated in adults and children with hemophilia B (congenital Factor IX deficiency) for:

- On-demand treatment and control of bleeding episodes,
- Perioperative management of bleeding,
- Routine prophylaxis to reduce the frequency of bleeding episodes.

Limitation of Use:

ALPROLIX is not indicated for induction of immune tolerance in patients with hemophilia B.

2 DOSAGE AND ADMINISTRATION

For intravenous use after reconstitution only

2.1 Dose

- Dose and duration of treatment depend on the severity of the Factor IX deficiency, the location and extent of bleeding, the individual patient's pharmacokinetic profile, and/or the patient's clinical condition.
- Patients may vary in their pharmacokinetic (e.g., half-life, in vivo recovery) and clinical responses. Base the dose and frequency of ALPROLIX on the individual clinical response.
- More frequent or higher doses may be needed in children <12 years of age, especially in children <6 years of age [see Use in Specific Populations (8.4)]. For patients 12 years of age or older, age-based dose adjustment is not usually required.
- In addition to the nominal (target) potency, the actual Factor IX potency in international units (IU), determined by the quality control laboratory at product release, is stated on each ALPROLIX vial label. ALPROLIX potency is assigned using a validated in vitro, activated partial thromboplastin time (aPTT)–based, one-stage clotting assay calibrated against the World Health Organization (WHO) international standard for Factor IX concentrates.
- Factor IX activity measurements in the clinical laboratory may be affected by the type of aPTT reagent or laboratory standard used [see Warnings and Precautions (5.4)].
  On average, one IU of ALPROLIX per kg body weight increases the circulating level of Factor IX by approximately 1% (IU/dL) in adults and children ≥6 years of age and by 0.6% (IU/dL) in children under 6 years of age. Estimate the required dose or the expected in vivo peak increase in Factor IX level expressed as IU/dL (or % of normal) using the following formulas:

IU/dL (or % of normal) = (Total Dose [IU]/Body Weight [kg]) × Recovery (IU/dL per IU/kg)
OR
Dose (IU) = Body Weight (kg) × Desired Factor IX Rise (IU/dL or, % of normal) × Reciprocal of Recovery (IU/kg per IU/dL)

- Consider determining the patient's in vivo recovery (in IU/dL per IU/kg) prior to elective major surgery and verify that the target Factor IX level has been achieved prior to major surgery and for major bleeds.

On-demand Treatment and Control of Bleeding Episodes

ALPROLIX dosing for on-demand treatment and control of bleeding episodes is provided in Table 1.

Table 1: Dosing Targets for Control of Bleeding Episodes
Type of Bleeding | Circulating Factor IX Level Required (IU/dL or % of normal) | Dosing Interval (hours)
Minor and Moderate For example: Uncomplicated hemarthroses, superficial muscle (except iliopsoas) without neurovascular compromise, superficial soft tissue, mucous membranes | 30–60 | Repeat every 48 hours if there is further evidence of bleeding.
Major For example: Iliopsoas and deep muscle with neurovascular injury, or substantial blood loss; Pharyngeal, retropharyngeal, retroperitoneal, CNS | 80–100 | Consider a repeat dose after 6–10 hours and then every 24 hours for the first 3 days. Due to the long half-life of ALPROLIX, the dose may be reduced and frequency of dosing may be extended after day 3 to every 48 hours or longer until bleeding stops and healing is achieved.

Perioperative Management of Bleeding

ALPROLIX dosing for perioperative management is provided in Table 2.

Table 2: Dosing Targets for Perioperative Management
Type of Surgery | Circulating Factor IX Level Required (IU/dL or % of normal) | Dosing Interval (hours)
Minor (including uncomplicated dental extraction) | 50–80 | A single infusion may be sufficient. Repeat as needed after 24–48 hours until bleeding stops and healing is achieved.
Major | 60–100 (initial level) | Consider a repeat dose after 6–10 hours and then every 24 hours for the first 3 days. Due to the long half-life of ALPROLIX, the dose may be reduced and frequency of dosing in the post-surgical setting may be extended after day 3 to every 48 hours or longer until bleeding stops and healing is achieved.

Routine Prophylaxis

- The recommended starting regimens for adults and adolescents ≥12 years of age are either 50 IU/kg once weekly, or 100 IU/kg once every 10 days.
- For children <12 years of age, start with 60 IU/kg once weekly.
- Adjust dosing regimen based on individual response. More frequent or higher doses may be needed in children <12 years of age, especially in children <6 years of age.

2.2 Reconstitution

1. Use aseptic technique (clean and germ-free) and a flat work surface during the reconstitution procedure.
2. Allow the vial of ALPROLIX, containing the white to off-white lyophilized powder and the prefilled diluent syringe to reach room temperature before use.
3. Remove the plastic cap from the vial and wipe the rubber stopper of the vial with an alcohol wipe. Allow the rubber stopper to dry.
4. Completely remove the backing from the vial adapter package by peeling back the lid. Do not remove the vial adapter from the package or touch the inside of the package of the adapter.
5. Place the vial on a flat surface and use one hand to hold the vial steady. Use the other hand to place the vial adapter over the vial. Place the adapter spike directly above the center of the rubber stopper and push the adapter straight down until the spike punctures the center of the vial stopper and is fully inserted.
6. Lift the package cover away from the vial adapter and discard the cover.
7. Hold the plunger rod at the circular disk. Place the tip of the plunger rod into the end of the syringe. Turn clockwise until it is securely attached. Only use the diluent syringe provided in the ALPROLIX package.
8. With one hand, hold the diluent syringe by the ridged part directly under the cap, with the cap pointing up. Do not use if the cap has been removed or is not securely attached.
9. With your other hand, grasp the cap and bend it at a 90° angle until it snaps off. After the cap snaps off, you will see the glass tip of the syringe. Do not touch the glass tip of the syringe or the inside of the cap.
10. With the vial sitting on a flat surface, insert the tip of the syringe into the adapter opening. Turn the syringe clockwise until it is securely attached to the adapter.
11. Slowly depress the plunger rod to inject all of the diluent into the vial. The plunger rod may rise slightly after this process. This is normal.
12. With the syringe still connected to the adapter, gently swirl the vial until the product is completely dissolved. The final solution should be clear to slightly opalescent and colorless. Do not shake. Do not use the reconstituted ALPROLIX if it contains visible particles or is cloudy.
13. Make sure the plunger rod is completely depressed. Turn the vial upside-down. Slowly pull on the plunger rod to draw the solution into the syringe. Be careful not to pull the plunger rod completely out of the syringe.
14. Gently unscrew the syringe from the vial adapter and dispose of the vial with the adapter still attached. Do not touch the syringe tip or the inside of the cap.
15. Use the reconstituted ALPROLIX as soon as possible, but no later than 3 hours after reconstitution. Protect from direct sunlight. Do not refrigerate after reconstitution.

To combine two or more vials of ALPROLIX, after step 12 above, follow these pooling steps:

1. Remove the diluent syringe from the vial adapter by turning it counterclockwise until it is completely detached. Do not detach the diluent syringe or the large luer lock syringe until ready to attach the large luer lock syringe to the next vial (with vial adapter attached).
2. Leave the vial adapter attached to the vial, as it is needed for attaching a large luer lock syringe.
3. Attach a separate, large luer lock syringe by turning clockwise until it is securely in place.
4. Slowly pull on the plunger rod to draw the solution into the syringe.
5. Repeat this pooling procedure with each vial necessary to obtain the required dose. Once you have pooled the required dose, proceed to administration using the large luer lock syringe.

2.3 Administration

For intravenous injection only

- Inspect the reconstituted ALPROLIX solution visually for particulate matter and discoloration prior to administration. Do not use if particulate matter or discoloration is observed.
- Do not administer reconstituted ALPROLIX in the same tubing or container with other medications.

Administration Steps:

1. Attach the syringe to the connector end of the infusion set tubing by turning clockwise until it is securely in place.
2. Depress the plunger until all air is removed from the syringe and ALPROLIX has reached the end of the infusion set tubing. Do not push ALPROLIX through the needle.
3. Remove the protective needle cover from the infusion set tubing.
4. Perform intravenous bolus infusion. The rate of administration should be determined by the patient's comfort level, and no faster than 10 mL per minute.

After infusing ALPROLIX, remove and properly discard the infusion set.

3 DOSAGE FORMS AND STRENGTHS

ALPROLIX is available as a white to off-white lyophilized powder in single-dose vials containing nominally (approximately) 250, 500, 1000, 2000, 3000, or 4000 international units (IU) of Factor IX potency per vial. The actual Factor IX potency is stated on each ALPROLIX vial.

4 CONTRAINDICATIONS

ALPROLIX is contraindicated in individuals who have a known history of hypersensitivity reactions, including anaphylaxis, to the product or its excipients (sucrose, mannitol, sodium chloride, L-histidine and polysorbate 20).

5 WARNINGS AND PRECAUTIONS

5.1 Hypersensitivity Reactions

Allergic-type hypersensitivity reactions, including anaphylaxis, have been reported with ALPROLIX.

The presence of inhibitors has been associated with allergic reactions with Factor IX replacement therapies, including with ALPROLIX. Evaluate patients experiencing allergic reactions for the presence of an inhibitor. Early signs of allergic reactions, which can progress to anaphylaxis, may include angioedema, chest tightness, hypotension, rash, nausea, vomiting, paresthesia, restlessness, wheezing and dyspnea. Discontinue use of ALPROLIX if hypersensitivity symptoms occur, and initiate appropriate treatment.

5.2 Neutralizing Antibodies

Formation of neutralizing antibodies (inhibitors) to Factor IX has been reported following administration of ALPROLIX. Monitor all patients regularly for the development of inhibitors by appropriate clinical observations and laboratory tests [see Warnings and Precautions (5.4)].

Evaluate patients experiencing allergic reactions for the presence of an inhibitor. Closely observe patients for signs and symptoms of acute hypersensitivity reactions, particularly during the early phases of exposure to the product.

Individuals with Factor IX inhibitors may be at an increased risk of anaphylaxis upon subsequent challenge with ALPROLIX.

5.3 Thromboembolic Complications

The use of Factor IX products has been associated with the development of thromboembolic complications, especially in individuals receiving continuous infusion through a central venous catheter. ALPROLIX should be administered as bolus infusion over several minutes [see Dosage and Administration (2.3)]. The safety of ALPROLIX administration by continuous infusion has not been studied.

5.4 Monitoring Laboratory Tests

- To confirm adequate Factor IX levels have been achieved and maintained, monitor patient plasma Factor IX levels by performing a validated one-stage clotting assay [see Dosage and Administration (2.1)]. Factor IX results can be affected by the type of aPTT reagent used. Measurement with a one-stage clotting assay using a kaolin-based aPTT reagent has been shown to result in an underestimation of Factor IX levels.
- Monitor for the development of Factor IX inhibitors if the expected Factor IX levels in patient plasma are not attained, or if bleeding is not controlled with the recommended dose of ALPROLIX. Perform a Bethesda assay to determine if Factor IX inhibitors are present.

5.5 Nephrotic Syndrome

Nephrotic syndrome has been reported following attempted immune tolerance induction in hemophilia B patients with Factor IX inhibitors and a history of allergic reactions to Factor IX. The safety and efficacy of using ALPROLIX for immune tolerance induction have not been established.

6 ADVERSE REACTIONS

The most common adverse reactions (incidence ≥1%) in previously untreated patients (PUPs) were injection site erythema, hypersensitivity, and Factor IX inhibition [see Warnings and Precautions (5.1), (5.2)]. The most common adverse reactions (incidence ≥1%) in previously treated patients (PTPs) were headache, oral paresthesia, and obstructive uropathy.

6.1 Clinical Trials Experience

Because clinical trials are conducted under widely varying conditions, adverse reaction rates observed in the clinical trials of a drug cannot be directly compared to rates in clinical trials of another drug and may not reflect the rates observed in clinical practice.

Previously Treated Patients (PTPs)

ALPROLIX has been evaluated in three completed studies (an adult and adolescent study, a pediatric study, and an extension study) in previously treated patients (PTPs) with severe to moderately severe hemophilia B (≤2% endogenous FIX activity). Of the 153 subjects treated, 30 (20%) were children (1 to 11 years of age), 11 (7%) were adolescents (12 to 17 years of age), and 112 (73%) were adults (18 to 71 years of age). There were 126 subjects (82.4%) treated for at least 52 weeks, 107 subjects (69.9%) for at least 104 weeks, and 67 (43.8%) treated for at least 208 weeks. The total number of exposure days (EDs) was 26,106 with a median of 165 (range 1–528) EDs per subject. Adverse events were monitored for a total of 561 subject-years.

Adverse reactions (ARs) were reported in 14 of 153 (9.2%) subjects treated with ALPROLIX. They are summarized in Table 3.

No subject was withdrawn from the trials due to an adverse reaction. In these PTP trials, no inhibitors were detected and no events of anaphylaxis or vascular thromboembolism were reported.

Table 3: Summary of Adverse Reactions in Previously Treated Patients
System Organ Class | Adverse Reactions | Number of Subjects (%) N=153 [153 previously treated patients (PTPs) treated with ALPROLIX from the adult and adolescent study, the pediatric study, and the extension study.]
Nervous system disorders | Headache Dizziness Dysgeusia | 2 (1.3) 1 (0.7) 1 (0.7)
Gastrointestinal disorders | Paresthesia oral Breath odor | 2 (1.3) 1 (0.7)
General disorders and administration site conditions | Fatigue Infusion site pain | 1 (0.7) 1 (0.7)
Cardiac disorders | Palpitations | 1 (0.7)
Renal and urinary disorders | Obstructive uropathy [Obstructive clot in the urinary collecting system of subjects with hematuria, that resolved with hydration.] | 2 (1.3)
 | Hematuria | 1 (0.7)
 | Renal colic | 1 (0.7)
Vascular disorders | Hypotension | 1 (0.7)
Metabolism and nutritional disorders | Decreased appetite | 1 (0.7)

Previously Untreated Patients (PUPs)

ALPROLIX safety was also evaluated in one completed study (PUPs study) in 33 subjects with hemophilia B (≤2% endogenous FIX activity). Overall, the median number of weeks on treatment was 83.01 (range: 6.7–226.7 weeks). The number of subjects with at least 10 EDs was 28 (84.8%), at least 20 EDs was 26 (78.8%), and at least 50 EDs was 21 (63.6%). The median number of EDs was 76 (range: 1–137) per subject.

Adverse events were monitored for a total of 57.51 subject-years. Adverse drug reactions were reported in 2 of 33 (6.1%) subjects treated with ALPROLIX. One subject (3.0%) in the PUP study developed the SAE of Factor IX inhibition and the same subject (3.0%) developed hypersensitivity. One additional subject (3.0%) in the PUP study developed injection site erythema.

Immunogenicity

Clinical trial subjects were monitored for neutralizing antibodies to Factor IX, and no inhibitors were detected in PTPs during the study. Of 33 PUPs, a total of 1 subject (3.0%) developed a low-titer neutralizing Factor IX inhibitor.

The detection of antibodies that are reactive to Factor IX is highly dependent on many factors, including the sensitivity and specificity of the assay, assay methodology, sample handling, timing of sample collection, concomitant medications and underlying disease. Therefore, it may be misleading to compare the incidence of antibodies to ALPROLIX with the incidence of antibodies to other products.

6.2 Postmarketing Experience

The following adverse reactions have been identified during the postapproval use of ALPROLIX. Because these reactions are reported voluntarily from a population of uncertain size, it is not always possible to reliably estimate their frequency or establish a causal relationship to drug exposure.

Blood and lymphatic system disorders: Factor IX inhibitor development

Immune system disorders: hypersensitivity, including anaphylaxis

For additional information, refer to the Warnings and Precautions 5.1 and 5.2.

8 USE IN SPECIFIC POPULATIONS

8.1 Pregnancy

Risk Summary

There are no studies of ALPROLIX use in pregnant women to inform a drug-associated risk.

The background risk of major birth defects and miscarriage for the indicated population is unknown; however, the background risk in the U.S. general population of major birth defects is 2%–4% and of miscarriage is 15%–20% of clinically recognized pregnancies.

Animal reproductive and developmental toxicity studies have not been conducted with ALPROLIX. In a placental transfer study, ALPROLIX was detected in murine fetal blood samples at approximately 2.6% of the maternal blood levels (range, 1.7% to 3.3%), 3 to 4 hours following dosing of pregnant mice with 3.3 to 6.6 times the clinical dose of 50 to 100 IU/kg ALPROLIX [see Data].

It is not known whether ALPROLIX can cause fetal harm when administered to a pregnant woman or can affect reproduction capacity. If ALPROLIX is clearly needed to treat a pregnant woman, advise the patient that the risks to the mother and to the fetus are unknown.

Data

Animal data

Pregnant, genetically-modified, FIX-deficient mice (HemB mice) were injected intravenously with a single dose of 330 IU/kg ALPROLIX at the end of pregnancy on Gestation Day 18, or with repeat doses of 330 IU/kg ALPROLIX on Gestation Days 18 and 20. Blood samples were collected from the maternal mice and the fetuses after dosing, and FIX activity was measured in both maternal and fetal plasma using a FIX chromogenic assay. After dosing pregnant HemB mice with ALPROLIX, FIX activity in fetal blood was approximately 2.6% of the maternal blood levels, suggesting that placental transfer of ALPROLIX may occur in pregnant female patients. The relevance of these data to humans is unknown.

8.2 Lactation

Risk Summary

It is not known whether ALPROLIX is excreted into human milk. There are no data available to assess the effects of ALPROLIX on milk production or the breastfed child.

The developmental and health benefits of breastfeeding should be considered along with the mother's clinical need for ALPROLIX and any potential adverse effects on the breastfed child from ALPROLIX or from the underlying maternal condition.

8.4 Pediatric Use

Safety, efficacy, and pharmacokinetics of ALPROLIX have been evaluated in previously treated patients (PTPs) from the adult and adolescent study (12 to <17 years of age) and from the pediatric study (1 to 11 years of age) [see Adverse Reactions (6), Clinical Trials Experience (6.1), Clinical Pharmacology (12.3) and Clinical Studies (14)]. Safety of ALPROLIX has been evaluated in previously untreated patients (PUPs) less than 18 years of age (median: 0.6 year; range: 0.08–2 years) in the PUPs study [see Adverse Reactions (6), Clinical Trials Experience (6.1), and Clinical Pharmacology (12.3)].

No dose adjustment is required for adolescents. Children under 12 years of age may have higher Factor IX body weight-adjusted clearance and lower recovery. More frequent or higher doses may be needed in children <12 years of age. When calculating target peak doses for treatment of bleeding or surgery, use the average in vivo recovery value of 0.6 IU/dL per IU/kg, or individually determined in vivo recovery, for children under 6 years of age [see Clinical Pharmacology (12.3)].

8.5 Geriatric Use

Clinical studies of ALPROLIX did not include a sufficient number of subjects age 65 and over to determine whether or not they respond differently than younger subjects.

11 DESCRIPTION

ALPROLIX is a sterile, non-pyrogenic, preservative-free, white to off-white, lyophilized powder for reconstitution with the diluent for intravenous injection. After reconstitution, the solution has a clear to slightly opalescent appearance and contains the excipients sucrose, mannitol, sodium chloride, L-histidine and polysorbate 20. ALPROLIX is available in single-dose vials containing nominally (approximately) 250 IU, 500 IU, 1000 IU, 2000 IU, 3000 IU, or 4000 IU of recombinant Factor IX. The actual potency determined by the quality control laboratory at product release is stated directly on each vial label.

Coagulation Factor IX (Recombinant), Fc Fusion Protein (rFIXFc), the active ingredient in ALPROLIX, is a recombinant coagulation Factor IX fusion protein consisting of the human coagulation Factor IX sequence covalently linked to the Fc domain of human immunoglobulin G1 (IgG1). The Factor IX portion of rFIXFc has a primary amino acid sequence that is identical to the Thr^148 allelic form of plasma derived Factor IX and has structural and functional properties similar to endogenous Factor IX. The Fc domain of rFIXFc contains the hinge, CH2, and CH3 regions of IgG1. rFIXFc contains 867 amino acids with a molecular weight of approximately 98 kilodaltons.

ALPROLIX is not derived from human blood and contains no preservatives. The recombinant Factor IX Fc fusion protein is expressed in a human embryonic kidney (HEK) cell line, which produces rFIXFc into a defined cell culture medium that does not contain proteins derived from animal or human sources. The purification process for rFIXFc does not include use of a monoclonal antibody reagent. To enhance viral safety, the production process also incorporates two dedicated viral clearance steps – a detergent treatment step for inactivation and a 15 nm filtration step for removal of viruses. The content of activated Factor IX Fc fusion protein (FIXaFc) is limited to ≤0.035 mole percent FIXaFc/FIXFc.

12 CLINICAL PHARMACOLOGY

12.1 Mechanism of Action

ALPROLIX is a recombinant, fusion protein that temporarily replaces the missing coagulation Factor IX needed for effective hemostasis. ALPROLIX contains the Fc region of human IgG1, which binds to the neonatal Fc receptor (FcRn). FcRn is part of a naturally occurring pathway that delays lysosomal degradation of immunoglobulins by cycling them back into circulation, and prolonging their plasma half-life.

12.2 Pharmacodynamics

Hemophilia B is a bleeding disorder characterized by a deficiency of functional coagulation Factor IX (FIX), which leads to a prolonged clotting time in the activated partial thromboplastin time (aPTT) assay, an established in vitro test for the biological activity of Factor IX. Treatment with ALPROLIX shortens the aPTT over the effective dosing period.

12.3 Pharmacokinetics

PK parameters for ALPROLIX were estimated based on the plasma FIX activity measured by the one-stage clotting assay.

Adults (≥18 Years)

The pharmacokinetics (PK) of ALPROLIX (rFIXFc) were evaluated in 22 adults (≥18 years of age) following a 10-minute intravenous infusion of a single dose of 50 IU/kg. Blood samples for PK analysis were collected prior to dosing and up to 240 hours (10 days) after dosing with 50 IU/kg. In addition, PK was assessed for 27 patients receiving the 100 IU/kg dose (Table 4). Blood samples were collected up to 336 hours after dosing. Table 4 presents the PK parameters in adults. The pharmacokinetics of ALPROLIX following single and repeat dosing (at week 26) were similar.

Table 4: Pharmacokinetic Parameters in Adults (arithmetic mean, %CV)
PK Parameters | ALPROLIX (50 IU/kg) (N=22) | ALPROLIX (100 IU/kg) (N=24)
Cmax (IU/dL) | 46 (68%) | 101 (20%)
AUCinf (h*IU/dL) | 1619 (26%) | 3964 (19%)
CL (mL/h/kg) | 3.3 (28%) | 2.6 (23%)
Vss (mL/kg) | 327 (28%) | 236 (24%)
Terminal T1/2 (h) | 86 (37%) | 97 (35%)
MRT (h) | 102 (30%) | 91 (23%)
IR (IU/dL per IU/kg) | 1.02 (59%) | 1.12 (22%)
Time to 1% FIX activity (d) | 12 (24%) | 16 (20%)
Abbreviations: CV = coefficient of variation; IR = incremental recovery; AUCinf = area under the FIX activity time curve to infinity; Terminal T1/2 = terminal phase elimination half-life; MRT = mean residence time; CL = body weight adjusted clearance; Vss = body weight adjusted volume of distribution at steady-state; Time to 1% FIX activity = estimated time in days after dose when FIX activity has declined to approximately 1 IU/dL above baseline

Adolescents (12 to 17 Years)

Pharmacokinetic parameters were evaluated following a 10-minute intravenous infusion in 11 evaluable adolescents (12 to 17 years of age) who received a single dose of 50 IU/kg or 100 IU/kg of ALPROLIX. Blood samples were collected prior to dosing and at multiple time points up to 336 hours (14 days) after dosing. PK parameters of ALPROLIX in adolescents are summarized in Table 5. The pharmacokinetics of ALPROLIX in adolescents are comparable with adults.

Pediatrics (2 to 10 Years)

In the pediatric study, pharmacokinetic parameters were evaluated following a 10-minute intravenous infusion in 24 evaluable children (2 to 10 years of age) who received a single 50 IU/kg dose of ALPROLIX. PK samples were collected prior to dosing and at multiple time points up to 168 hours (7 days) after dosing.

Table 5 presents the PK parameters in adolescents and children. Compared to adults, incremental recovery was lower and body weight adjusted clearance was higher in children under 12 years of age, particularly in children under 6 years of age. Incremental recovery in children 2 to 4 years and 6 to 10 years was lower by 41% and 27%, respectively. Compared to adults, body weight-adjusted clearance in children 2 to 4 years and 6 to 10 years was higher by 36% and 11%, respectively. This may result in a need for per kg body weight dose and/or interval adjustments in children under 12 years of age [see Use in Specific Populations (8.4)].

Table 5: Pharmacokinetic Parameters of ALPROLIX in Children and Adolescents following 50 IU/kg or 100 IU/kg Dose (arithmetic mean, %CV)
PK Parameters | <6 years (range: 2 to 4 years) (N=11, 50 IU/kg) | 6 to <12 years (range: 6 to 10 years) (N=13, 50 IU/kg) | 12 to 17 years (N=8, 50 IU/kg) | 12 to 17 years (N=3, 100 IU/kg)
Cmax (IU/dL) | 30 (19%) | 37 (29%) | 43 (44%) | 96 (9%)
IR (IU/dL per IU/kg) | 0.60 (20%) | 0.74 (29%) | 0.87 (44%) | 0.96 (10%)
AUCinf (h*IU/dL) | 1169 (15%) | 1471 (27%) | 1439 (24%) | 3420 (13%)
Terminal T½ (h) | 68 (24%) | 72 (23%) | 80 (15%) | 94 (24%)
MRT (h) | 86 (23%) | 84 (19%) | 95 (17%) | 95 (29%)
CL (mL/h/kg) | 4.4 (17%) | 3.6 (25%) | 3.7 (26%) | 3.0 (12%)
Vss (mL/kg) | 373 (23%) | 302 (29%) | 345 (24%) | 275 (20%)
Abbreviations: CV = Coefficient of Variation; IR = incremental recovery; AUCinf = area under the FIX activity time curve to infinity; Terminal T ½= terminal phase elimination half-life; MRT = mean residence time; CL = body weight adjusted clearance; Vss = body weight adjusted volume of distribution at steady-state

13 NONCLINICAL TOXICOLOGY

13.1 Carcinogenesis, Mutagenesis, Impairment of Fertility

Long-term studies in animals to evaluate the carcinogenic potential of ALPROLIX, or studies to determine the effects of ALPROLIX on genotoxicity or fertility have not been performed. An assessment of the carcinogenic potential of ALPROLIX was completed and no carcinogenic risk from product use has been identified.

14 CLINICAL STUDIES

The safety and efficacy of ALPROLIX was evaluated in a multi-center, prospective, open-label study in previously treated patients (PTPs): adult and adolescent patients 12 to 71 years of age and a study in pediatric patients 1 to 11 years of age.

Adult and Adolescent Study (12 to 71 Years)

The non-randomized adult and adolescent study compared each of two prophylactic treatment regimens (fixed weekly and individualized interval) to episodic (on-demand) treatment; determined hemostatic efficacy in the treatment of bleeding episodes; and determined hemostatic efficacy during perioperative management of subjects undergoing major surgical procedures. A total of 123 previously treated patients (PTPs) with severe to moderately severe hemophilia B (≤2% endogenous FIX activity) were followed for up to 77 weeks. Subjects who were on prophylaxis before the study were assigned to one of the prophylaxis arms. Subjects who were treating on-demand before the study were assigned to either one of the two prophylaxis arms or to the on-demand treatment arm. Treatment arm assignments were based on standard of care and discussion between the investigator and the subject.

Sixty-three subjects in the fixed weekly interval arm received ALPROLIX for routine prophylaxis starting at an initial dose of 50 IU/kg. The dose was adjusted to maintain FIX trough level between 1% and 3% above baseline or higher, as clinically indicated to prevent bleeding. Fifty subjects (79%) required at least one dose adjustment and the median number of dose adjustments was one. The overall median dose on study was 45.2 IU/kg (interquartile range: 38.1, 53.7). The median weekly dose during the last 6 months on study in 58 subjects who were on study for at least 9 months was 40.7 IU/kg (interquartile range: 32.3, 54.1).

Twenty-nine subjects in the individualized interval arm initially received ALPROLIX for routine prophylaxis at a dose of 100 IU/kg every 10 days, with the interval adjusted to maintain FIX trough level between 1% and 3% above baseline or higher, as clinically indicated to prevent bleeding. The overall median interval on study was 12.5 days (interquartile range: 10.4, 13.4). The median interval during the last 6 months in 26 subjects who were on study for at least 9 months was 13.8 days (interquartile range: 10.5, 14.0).

Twenty-seven subjects received ALPROLIX as needed for the treatment of bleeding episodes in the episodic (on-demand) treatment arm.

Twelve subjects received ALPROLIX for perioperative management in 14 major surgical procedures. Major surgery was defined as any surgical procedure with or without general anesthesia in which a major body cavity was penetrated and exposed, or a substantial impairment of physical or physiological functions was produced. Four subjects in this arm did not participate in the other arms.

Pediatric Study (1 to 11 Years)

The pediatric study enrolled a total of 30 previously treated male pediatric patients with severe to moderately severe hemophilia B (≤2% endogenous FIX activity). Subjects were less than 12 years of age (15 were 1 to 5 years of age and 15 were 6 to 11 years of age). All subjects received treatment with ALPROLIX and were followed for up to 52 weeks.

All 30 subjects were treated with ALPROLIX on an individualized prophylactic dose regimen starting with 50–60 IU/kg every 7 days, with adjustment of dose to a maximum of 100 IU/kg and dosing interval adjusted between once and twice weekly. The median dosing interval was 7.0 days (interquartile range: 6.9 to 7.0) with no difference between the age cohorts. The median average weekly dose of ALPROLIX was 59.4 IU/kg and (interquartile range: 53.0 to 64.8) for subjects 1 to 5 years of age and 57.8 IU/kg (interquartile range: 51.7 to 65.0) for subjects 6 to 11 years of age. At the end of the trial, the median prescribed once weekly prophylactic dose was 60 IU/kg across both pediatric age subgroups (range: 40 to 70 IU/kg).

On-demand Treatment and Control of Bleeding Episodes

Adult and adolescent study (12 to 71 years)

A total of 636 bleeding events were observed by 114 subjects in the fixed weekly interval prophylaxis, individualized interval prophylaxis, and the episodic (on-demand) arms. The median total dose to treat a bleeding episode was 47.0 IU/kg (interquartile range: 33.3, 62.5). Assessment of response to each injection was recorded by subjects at 8–12 hours after treatment. Efficacy in control of bleeding episodes is summarized in Table 6.

Table 6: Efficacy in Control of Bleeding in Adults and Adolescents
Bleeding Episodes | (N=636)
Number of injections to treat bleeding episodes
1 injection | 575 (90.4%)
2 injections | 44 (6.9%)
3 injections | 17 (2.7%)
Response to first injection [Excellent: abrupt pain relief and/or improvement in signs of bleeding; Good: definite pain relief and/or improvement in signs of bleeding but possibly requiring another injection in 1–2 days; Moderate: probable or slight beneficial effect and requiring more than one injection; None: no improvement, or worsening. Response evaluated at approximately 8 hours after treatment.] | (N=613)
Excellent or good | 513 (83.7%)
Moderate | 90 (14.7%)
None | 10 (1.6%)

Pediatric study (1 to 11 years)

A total of 60 bleeding events were observed by 20 subjects during the study. The median total dose to treat a bleeding episode was 68.2 IU/kg (interquartile range: 50.9, 126.2). Assessment of response to each injection was recorded by subjects at 8 to 12 hours post treatment. Efficacy in control of bleeding episodes is summarized in Table 7.

Table 7: Efficacy in Control of Bleeding in Pediatric Subjects
 | 1 to 5 Years | 6 to 11 Years | Total (1 to 11 Years)
Bleeding episodes | (N=22) | (N=38) | (N=60)
Number of injections to treat bleeding episodes
1 injection | 19 (86.4%) | 26 (68.4%) | 45 (75.0%)
2 injections | 2 (9.1 %) | 8 (21.1%) | 10 (16.7%)
3 injections | 1 (4.5%) | 4 (10.5%) | 5 (8.3%)
Response to first injection [Seven first injections for bleeding episodes were not evaluated for response and are excluded from this analysis. Excellent: abrupt pain relief and/or improvement in signs of bleeding; Good: definite pain relief and/or improvement in signs of bleeding but possibly requiring another injection in 1–2 days; Moderate: probable or slight beneficial effect and requiring more than one injection; None: no improvement, or worsening. Response evaluated at approximately 8 hours after treatment.] | (N=53)
Excellent or good | 47 (88.7%)
Moderate | 5 (9.4%)
None | 1 (1.9%)

Perioperative Management

Thirty-five major surgical procedures were performed in 22 subjects (age range: 10–63 years) in the adult and adolescent study and in the extension study. Of the 35 major surgeries, 28 surgeries (80.0%) required a single perioperative dose to maintain hemostasis during surgery. The median average dose per injection to maintain hemostasis during surgery was 94.7 IU/kg (range: 49 to 152). Perioperative Factor IX replacement with ALPROLIX was by bolus infusion only. The safety of continuous infusion was not evaluated.

Hemostasis was assessed by the investigator after surgery. Assessment of intraoperative and postoperative hemostatic response for major surgeries in the adult and adolescent study and the ongoing extension study are summarized in Table 8.

Table 8: Summary of Hemostatic Response for Major Surgery
 |  | Response
Major Surgery | Number of Procedures (Number of Subjects) [8 subjects had more than one major surgery] | Excellent | Good | Fair | Poor/None
Ablation of Liver Lesion | 1 (1) | 1
Arthroscopy | 2 (2) | 2
Closure of Rectal Fistula | 1 (1) | 1
Craniotomy [Two surgeries were not assessed for response] | 1 (1) | 1
Dental Abscess | 1 (1) | 1
Finger Amputation or Partial Amputation | 2 (1) | 2
Hip Replacement or Repair | 2 (2) | 1 | 1
Install or Removal of External Ilizarov Fixation | 2 (1) | 2
Liver Transplant | 1 (1) | 1
Liver Resection | 1 (1) | 1
Orchiectomy | 1 (1) | 1
Percutaneous-Ablation of Hepatic Carcinoma | 1 (1) | 1
Patellar Resurfacing | 1 (1) | 1
Pilonidal Cyst | 1 (1) | 1
Pin Release | 1 (1) | 1
Spinal Surgery | 1 (1) | 1
Tendon Transfer in Right Arm | 1 (1) | 1
Tonsillectomy | 1 (1) | 1
Unilateral Ankle Fusion | 2 (2) | 2
Unilateral Ankle Replacement or Revision | 1 (1) | 1
Unilateral Knee Replacement or Revision | 8 (8) | 6 | 2

There were an additional 62 minor surgical procedures in 37 subjects in the adult and adolescent study, the pediatric study, and the extension study. Hemostatic response was assessed for 38 minor surgeries; 36 minor surgeries were rated as excellent or good and 2 as fair.

Routine Prophylaxis

Adult and adolescent study (12 to 71 years)

Using a negative binomial model, a reduction in annualized bleeding rate (ABR) of 83% (76%–89%) for subjects in the fixed weekly interval arm and a reduction of 87% (80%–92%) for subjects in the individualized interval arm compared to the episodic (on-demand) treatment arm was observed.

The median duration of treatment on study was 51.4 weeks (range <1–77). A comparison of the ABRs in subjects evaluable for efficacy is summarized in Table 9.

Table 9: Median Annualized Bleeding Rate (ABR) by Treatment Arm in Adults and Adolescents
Bleeding Episodes | Prophylaxis Fixed Weekly Interval (N=61) | Prophylaxis Individualized Interval (N=26) | Episodic (On-Demand) (N=27)
Overall ABR (IQR) [IQR = interquartile range] | 2.95 (1.01, 4.35) | 1.38 (0.00, 3.43) | 17.69 (10.77, 23.24)
Spontaneous ABR (IQR) | 1.04 (0.00, 2.19) | 0.88 (0.00, 2.30) | 11.78 (2.62, 19.78)
Joint ABR (IQR) | 1.11 (0.00, 4.01) | 0.36 (0.00, 3.24) | 13.58 (6.13, 21.61)

Pediatric study (1 to 11 years)

The median duration of treatment on study was 49.4 weeks (range 12–52). A comparison of the median ABRs in pediatric subjects evaluable for efficacy is summarized in Table 10.

Table 10: Median Annualized Bleeding Rate (ABR) in Pediatric Subjects
Bleeding Episodes | 1 to 5 Years (N=15) | 6 to 11 Years (N=15) | Total (<12 Years) (N=30)
Overall ABR (IQR) [IQR=interquartile range] | 1.09 (0.00, 2.90) | 2.13 (0.00, 4.17) | 1.97 (0.00, 3.13)
Spontaneous ABR (IQR) | 0.00 (0.00, 1.09) | 0.00 (0.00, 2.09) | 0.00 (0.00, 1.16)
Joint ABR (IQR) | 0.00 (0.00, 0.00) | 1.06 (0.00, 2.09) | 0.00 (0.00, 1.12)

16 HOW SUPPLIED/STORAGE AND HANDLING

How Supplied

ALPROLIX is supplied as a kit comprising:

- one single-dose glass vial containing rFIXFc powder,
- one prefilled syringe containing 5 mL diluent and sealed with a plunger stopper and tip-cap, and
- one sterile vial adapter (reconstitution device).

ALPROLIX is available in 250 IU, 500 IU, 1000 IU, 2000 IU, 3000 IU or 4000 IU nominal (approximate) dosage strengths. The actual Factor IX potency, expressed in IU, is stated on each rFIXFc vial and carton label. Not made with natural rubber latex.

Nominal (Approximate) Strength | Potency Color Code | Kit NDC Number
250 IU | Yellow | 71104-966-01
500 IU | Blue | 71104-911-01
1000 IU | Green | 71104-922-01
2000 IU | Red | 71104-933-01
3000 IU | Grey | 71104-944-01
4000 IU | Orange | 71104-977-01

Storage and Handling

- Store ALPROLIX in the original package in order to protect it from light.
- Store ALPROLIX at 2°C to 8°C (36°F to 46°F). Do not freeze. Freezing will damage the prefilled diluent syringe.
- ALPROLIX can be stored at room temperature, not to exceed 30°C (86°F), for a single period of up to 6 months within the expiration date printed on the carton and vial label. If stored at room temperature, record the date on the carton when the product was removed from refrigeration. Use the product before the end of this 6-month period or discard it. Do not place the product back into refrigeration after warming to room temperature. The shelf-life then expires after storage at room temperature for 6 months, or after the expiration date on the product vial, whichever is earlier.
- Do not use product or diluent after the expiration date printed on the carton, vial, or syringe.
- Reconstituted product may be stored at room temperature, not to exceed 30°C (86°F) for no longer than 3 hours. Protect from direct sunlight. Discard any product not used within 3 hours after reconstitution.

17 PATIENT COUNSELING INFORMATION

Advise the patient to:

- Read the FDA-approved patient labeling (Patient Information and Instructions for Use).
- Report any adverse reactions or problems following ALPROLIX administration to their physician or healthcare provider.
- Contact their healthcare provider or treatment facility for further treatment and/or assessment if they experience a lack of a clinical response to Factor IX therapy, as this may indicate the development of an inhibitor [see Warnings and Precautions (5.2)].
- Discontinue use of the product and contact their healthcare provider if early signs of hypersensitivity reactions (including hives, chest tightness, wheezing, difficulty breathing, and swelling of the face) and anaphylaxis occur. [see Warnings and Precautions (5.1)].
- Contact their healthcare provider or seek emergency care immediately if a thrombotic/thromboembolic event should occur [see Warnings and Precautions (5.3)].

Manufactured by:
Bioverativ Therapeutics Inc.
Waltham, MA 02451
A SANOFI COMPANY
US License Number 2078

©2023 Bioverativ Therapeutics Inc. All rights reserved.

For patent information: https://www.sanofi.us/en/products-and-resources/patents

Patient Information

ALPROLIX® /all' prō liks /

[Coagulation Factor IX (Recombinant), Fc Fusion Protein]

Please read this Patient Information carefully before using ALPROLIX and each time you get a refill, as there may be new information. This Patient Information does not take the place of talking with your healthcare provider about your medical condition or your treatment.

What is ALPROLIX?

ALPROLIX is an injectable medicine that is used to help control and prevent bleeding in people with hemophilia B. Hemophilia B is also called congenital Factor IX deficiency.

Your healthcare provider may give you ALPROLIX when you have surgery.

Who should not use ALPROLIX?

You should not use ALPROLIX if you are allergic to ALPROLIX or any of the other ingredients in ALPROLIX. Tell your healthcare provider if you have had an allergic reaction to any Factor IX product prior to using ALPROLIX.

What should I tell my healthcare provider before using ALPROLIX?

Tell your healthcare provider about all of the medicines you take, including all prescription and non-prescription medicines, such as over-the-counter medicines, supplements, or herbal medicines.

Tell your doctor about all of your medical conditions, including if you:

- are pregnant or planning to become pregnant. It is not known if ALPROLIX may harm your unborn baby.
- are breastfeeding. It is not known if ALPROLIX passes into breast milk or if it can harm your baby.
- have been told that you have inhibitors to Factor IX (because ALPROLIX may not work for you).

How should I use ALPROLIX?

ALPROLIX should be administered as ordered by your healthcare provider. You should be trained on how to do infusions by your healthcare provider. Many people with hemophilia B learn to infuse their ALPROLIX by themselves or with the help of a family member.

See the Instructions for Use for directions on infusing ALPROLIX. The steps in the Instructions for Use are general guidelines for using ALPROLIX. Always follow any specific instructions from your healthcare provider. If you are unsure of the procedure, please ask your healthcare provider. Do not use ALPROLIX as a continuous intravenous infusion.

Contact your healthcare provider immediately if bleeding is not controlled after using ALPROLIX.

What are the possible side effects of ALPROLIX?

Common side effects of ALPROLIX include headache, abnormal sensation in the mouth, and pain in your side with blood in your urine, which may be a sign of clot formation in the urinary collecting system.

Allergic reactions may occur. Call your healthcare provider or get emergency treatment right away if you have any of the following symptoms: hives, chest tightness, wheezing, difficulty breathing, or swelling of the face.

Redness to the skin at the injection site may also occur.

ALPROLIX may increase the risk of forming abnormal blood clots in your body, especially if you have risk factors for developing blood clots. Call your healthcare provider or seek emergency care if you have symptoms of a possible abnormal blood clot, which may include: chest pain, difficulty breathing, unexpected swelling of an arm or leg with or without pain or tenderness.

Your body can also make antibodies called "inhibitors" against ALPROLIX, which may stop ALPROLIX from working properly. Your healthcare provider may need to test your blood for inhibitors from time to time.

These are not all the possible side effects of ALPROLIX.

Talk to your healthcare provider about any side effect that bothers you or that does not go away.

How should I store ALPROLIX?

Store ALPROLIX vials at 2°C to 8°C (36°F to 46°F). Do not freeze.

ALPROLIX vials may also be stored at room temperature up to 30°C (86°F) for a single 6-month period.

If you choose to store ALPROLIX at room temperature:

- Note on the carton the date on which the product was removed from refrigeration.
- Use the product before the end of this 6-month period or discard it.
- Do not return the product to the refrigerator.

Do not use product or diluent after the expiration date printed on the carton, vial, or syringe.

After Reconstitution:

- Use the reconstituted product as soon as possible; however, you may store the reconstituted product at room temperature up to 30°C (86°F) for up to 3 hours. Protect the reconstituted product from direct sunlight. Discard any product not used within 3 hours after reconstitution.
- Do not use ALPROLIX if the reconstituted solution is cloudy, contains particles or is not colorless.

What else should I know about ALPROLIX?

Medicines are sometimes prescribed for purposes other than those listed here. Do not use ALPROLIX for a condition for which it was not prescribed. Do not share ALPROLIX with other people, even if they have the same symptoms that you have.

This Patient Information has been approved by the US Food and Drug Administration.

Manufactured by:
Bioverativ Therapeutics Inc.
Waltham, MA 02451
A SANOFI COMPANY
US License Number 2078

©2023 Bioverativ Therapeutics Inc. All rights reserved.

Revised: May 2023

INSTRUCTIONS FOR USE

ALPROLIX®

Coagulation Factor IX (Recombinant), Fc Fusion Protein

INSTRUCTIONS FOR USE

Read the Instructions for Use before you start using ALPROLIX® and each time you get a refill. There may be new information. This information does not take the place of talking to your healthcare provider about your medical condition or your treatment.

Your healthcare provider should show you or your caregiver how to reconstitute and administer ALPROLIX the first time ALPROLIX is used.

Check the expiration date on the ALPROLIX kit.

Do not use the product if past the expiration date.

Allow the ALPROLIX vial and the diluent to come to room temperature.

Do not use external heat sources such as putting the vial and/or diluent in hot water.

Find a clean, flat work surface and collect all the supplies you will need to reconstitute and administer ALPROLIX.

Wash your hands with soap and water. Aseptic technique (clean and germ free) should be used.

YOUR KIT CONTAINS:

RECONSTITUTION

Step 1
Remove the plastic cap from the ALPROLIX vial.
Wipe the rubber stopper of the vial with an alcohol wipe and allow it to dry.
After cleaning, do not touch the rubber stopper with your hand or allow it to touch any surface.

Step 2
Completely remove the backing from the vial adapter package by peeling back the lid.
Do not remove the vial adapter from the package or touch the inside of the vial adapter.

Step 3
Keep the vial on a flat surface. Hold the vial adapter package with one hand and using the other hand, place the vial adapter over the vial.
The spike should be placed directly above the center of the rubber stopper.
Push the vial adapter straight down until the adapter spike punctures the center of the vial stopper and is fully inserted.

Step 4
Lift the package cover away from the vial adapter and discard the cover.

Step 5
Only use the diluent syringe provided to reconstitute the drug product.
Hold the plunger rod at the circular disk.
Place the tip of the plunger rod into the end of the syringe.
Turn in a clockwise motion until it is securely attached.

Step 6
With one hand, hold the diluent syringe right under the cap, and with the cap pointing up.
Make sure you are holding the diluent syringe by the ridged part directly under the cap.
Do not use if the cap has been removed or is not securely attached.

Step 7
With your other hand, grasp the cap and bend it at a 90° angle until it snaps off.
After the cap snaps off, you will see the glass tip of the syringe.
Do not touch the glass tip of the syringe or inside of the cap.

Step 8
Be sure the vial is sitting on a flat surface.
Insert the tip of the syringe into the adapter opening.
Turn the syringe in a clockwise motion until it is securely attached to the adapter.

Step 9
Slowly depress the plunger rod to inject all of the diluent into the vial.
The plunger rod may rise slightly after this process. This is normal.

Step 10
With the syringe still connected to the adapter, gently swirl the vial until the product is completely dissolved.
The appearance of the solution should be clear to slightly opalescent and colorless.
Do not shake.
Do not use the reconstituted ALPROLIX if it contains visible particles or is cloudy.
If you are using more than one vial, stop here and proceed to the Pooling Instructions on the back.

Step 11
Make sure the plunger rod is completely depressed.
Turn the vial upside-down.
Slowly pull on the plunger rod to draw the solution into the syringe.
Be careful not to pull the plunger rod completely out of the syringe.

Step 12
Gently unscrew the syringe from the vial adapter and dispose of the vial with the adapter still attached.
Do not touch the syringe tip or the inside of the cap.
Reconstituted ALPROLIX should be administered as soon as possible.

TURN OVER FOR POOLING AND ADMINISTRATION

TURN OVER TO FRONT SIDE FOR RECONSTITUTION

POOLING

POOLING is the process of combining two or more reconstituted vials into a larger syringe (not into the diluent syringe) prior to intravenous administration.

If you are using two or more vials, follow these pooling steps.

Be sure to leave the vial adapter attached to the vial as you will need it for attaching a large luer lock syringe.

Do not detach the diluent syringe or the large luer syringe until you are ready to attach the large luer lock syringe to the next vial (with vial adapter attached).

Step 1
Remove the diluent syringe from the vial adapter by turning it counterclockwise until it is completely detached.

Step 2
Attach a separate large luer lock syringe by turning clockwise until it is securely attached.

Step 3
Slowly pull on the plunger rod to draw the solution into the syringe.
Repeat this pooling procedure with each vial you will be using.
Once you have pooled the required dose, proceed to administration using the large luer lock syringe.

ADMINISTRATION (Intravenous Injection)

ALPROLIX is administered by intravenous infusion after reconstitution of the drug powder with the diluent.

Your healthcare provider should teach you how to infuse ALPROLIX. Once you have been taught to self-infuse, you can follow these instructions.

Do not administer reconstituted ALPROLIX if it contains particulate matter, is discolored, or is cloudy.

Step 1
Attach the syringe to the connector end of the infusion set tubing by turning clockwise until it is securely attached.
Do not administer reconstituted ALPROLIX in the same tubing or container with other medicinal products.

Step 2
Apply a tourniquet and clean the skin area where you will perform the infusion using an alcohol wipe.

Step 3
Depress the plunger until all air is removed from the syringe and ALPROLIX has reached the end of the infusion set tubing.
Do not push ALPROLIX through the needle.

Step 4
Remove the protective needle cover from the infusion set tubing.
Insert the needle on the infusion set tubing into the vein.
Remove the tourniquet.
Always verify proper needle placement when performing intravenous administration.

Step 5
Slowly depress the plunger on the syringe to administer ALPROLIX.
ALPROLIX should be injected intravenously over several minutes.
The rate of administration should be determined by your comfort level.
The small amount of drug product left in the infusion set will not affect treatment.

Step 6
After infusing ALPROLIX, remove the infusion set and use a sterile gauze to put pressure on the infusion site for several minutes.
Apply an adhesive bandage if necessary.
Dispose of all unused solution, empty vial(s), and other used medical supplies in an appropriate medical waste container.

STORAGE CONDITIONS - PRODUCT KIT

Keep refrigerated until use.
Keep away from direct sunlight.

STORAGE CONDITIONS - RECONSTITUTED

ALPROLIX should be administered within 3 hours after reconstitution.

Do not refrigerate after reconstitution.

Keep away from direct sunlight.

This Instructions for Use has been approved by the US Food and Drug Administration.

Manufactured by:
Bioverativ Therapeutics Inc.
Waltham, MA 02451
A SANOFI COMPANY
US License Number 2078
©2023 Bioverativ Therapeutics Inc. All rights reserved.

For more information go to www.ALPROLIX.com or call 1-855-692-5776

Revised: May 2023

PRINCIPAL DISPLAY PANEL - Kit Carton - 500 IU

500 IU Nominal

NDC 71104-911-01

One single-use vial
with 5 mL prefilled
diluent syringe

ALPROLIX®

Coagulation Factor IX
(Recombinant), Fc Fusion Protein

For Intravenous Administration

Rx Only

Manufactured by:
Bioverativ Therapeutics Inc.
Waltham, MA 02451
US License Number 2078

www.ALPROLIX.com

Bioverativ®

PRINCIPAL DISPLAY PANEL - Kit Carton - 1000 IU

1000 IU Nominal

NDC 71104-922-01

One single-use vial
with 5 mL prefilled
diluent syringe

ALPROLIX®

Coagulation Factor IX
(Recombinant), Fc Fusion Protein

For Intravenous Administration

Rx Only

Manufactured by:
Bioverativ Therapeutics Inc.
Waltham, MA 02451
US License Number 2078

www.ALPROLIX.com

Bioverativ®

PRINCIPAL DISPLAY PANEL - Kit Carton - 2000 IU

2000 IU Nominal

NDC 71104-933-01

One single-use vial
with 5 mL prefilled
diluent syringe

ALPROLIX®

Coagulation Factor IX
(Recombinant), Fc Fusion Protein

For Intravenous Administration

Rx Only

Manufactured by:
Bioverativ Therapeutics Inc.
Waltham, MA 02451
US License Number 2078

www.ALPROLIX.com

Bioverativ®

PRINCIPAL DISPLAY PANEL - Kit Carton - 3000 IU

3000 IU Nominal

NDC 71104-944-01

One single-use vial
with 5 mL prefilled
diluent syringe

ALPROLIX®

Coagulation Factor IX
(Recombinant), Fc Fusion Protein

For Intravenous Administration

Rx Only

Manufactured by:
Bioverativ Therapeutics Inc.
Waltham, MA 02451
US License Number 2078

www.ALPROLIX.com

Bioverativ®

PRINCIPAL DISPLAY PANEL - Kit Carton - 250 IU

250 IU Nominal

NDC 71104-966-01

One single-use vial
with 5 mL prefilled
diluent syringe

ALPROLIX®

Coagulation Factor IX
(Recombinant), Fc Fusion Protein

For Intravenous Administration

Rx Only

Manufactured by:
Bioverativ Therapeutics Inc.
Waltham, MA 02451
US License Number 2078

www.ALPROLIX.com

Bioverativ®

PRINCIPAL DISPLAY PANEL - Kit Carton - 4000 IU

4000 IU Nominal

NDC 71104-977-01

One single-use vial
with 5 mL prefilled
diluent syringe

ALPROLIX®

Coagulation Factor IX
(Recombinant), Fc Fusion Protein

For Intravenous Administration

Rx Only

Manufactured by:
Bioverativ Therapeutics Inc.
Waltham, MA 02451
US License Number 2078

www.ALPROLIX.com

Bioverativ®